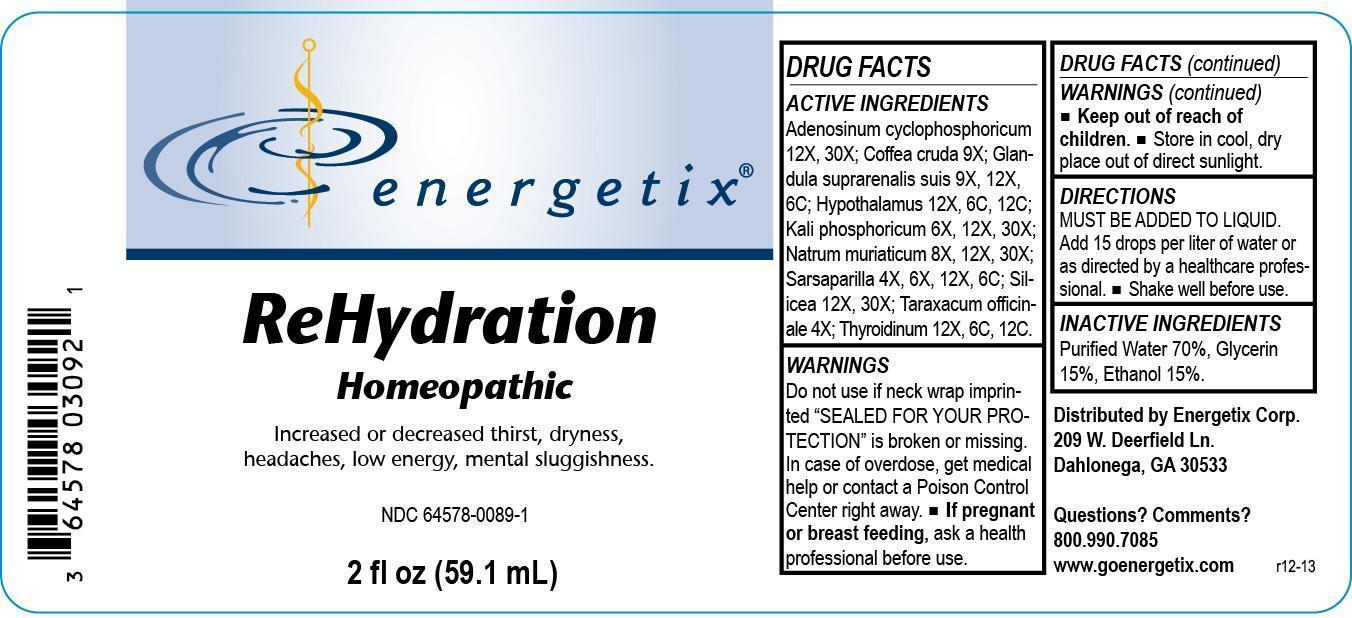 DRUG LABEL: ReHydration
NDC: 64578-0089 | Form: LIQUID
Manufacturer: Energetix Corp
Category: homeopathic | Type: HUMAN PRESCRIPTION DRUG LABEL
Date: 20140113

ACTIVE INGREDIENTS: ADENOSINE CYCLIC PHOSPHATE 12 [hp_X]/59.1 mL; ARABICA COFFEE BEAN 9 [hp_X]/59.1 mL; SUS SCROFA ADRENAL GLAND 9 [hp_X]/59.1 mL; BOS TAURUS HYPOTHALAMUS 12 [hp_X]/59.1 mL; POTASSIUM PHOSPHATE, DIBASIC 6 [hp_X]/59.1 mL; SODIUM CHLORIDE 8 [hp_X]/59.1 mL; SARSAPARILLA 4 [hp_X]/59.1 mL; SILICON DIOXIDE 12 [hp_X]/59.1 mL; TARAXACUM OFFICINALE 4 [hp_X]/59.1 mL; THYROID, UNSPECIFIED 12 [hp_X]/59.1 mL
INACTIVE INGREDIENTS: WATER 41.362884 mL/59.1 mL; GLYCERIN 8.863475 mL/59.1 mL; ALCOHOL 8.863475 mL/59.1 mL

ReHydration

ACTIVE INGREDIENT

Adenosinum cyclophosphoricum 12X, 30X; Coffea cruda 9X; Glandula suprarenalis suis 9X, 12X ,6C; Hypothalamus 12X, 6C, 12C; Kali phosphoricum 6X, 12X, 30X; Natrum muriaticum 8X, 12X, 30X; Sarsaparilla 4X, 6X, 12X, 6C; Silicea 12X, 30X; Taraxacum officinale 4X; Thyroidinum 12X, 6C, 12C.

Do not use if neck wrap imprinted "SEALED FOR YOUR PROTECTION" is broken or missing.

OVERDOSAGE

In case of overdose, get medical help or contact a Poison Control Center right away.

PREGNANCY OR BREAST FEEDING

If pregnant or breast feeding, ask a health professional before use.

Keep out of reach of children.

STORAGE AND HANDLING

Store in cool, dry place out of direct sunlight.

Questions? Comments?

800.990.7085 www.goenergetix.com

PURPOSE

Increased or decreased thirst, dryness, headaches, low energy, mental sluggishness.

INACTIVE INGREDIENT

Purified Water 70%, Glycerin 15%, Ethanol 15%.

DOSAGE AND ADMINISTRATION

MUST BE ADDED TO LIQUID. Add 15 drops per liter of water or as directed by a healthcare professional. Shake well before use.

INDICATIONS AND USAGE

Increased or decreased thirst, dryness, headaches, low energy, mental sluggishness.